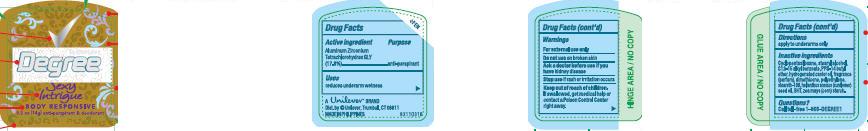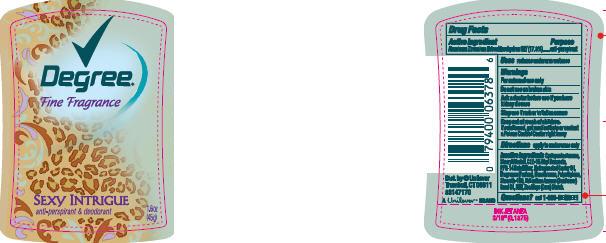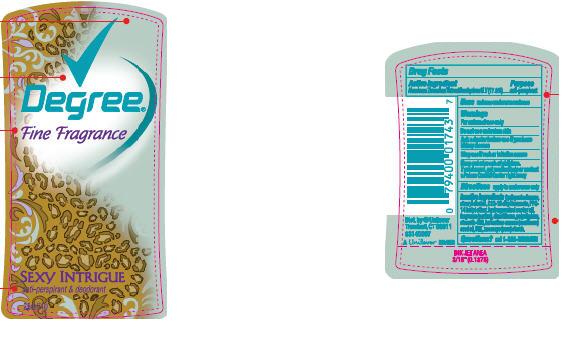 DRUG LABEL: Degree For Women Sexy Intrique
NDC: 64942-1065 | Form: STICK
Manufacturer: Conopco Inc. d/b/a Unilever
Category: otc | Type: HUMAN OTC DRUG LABEL
Date: 20100203

ACTIVE INGREDIENTS: Aluminum Zirconium Tetrachlorohydrex GLY 17.8 g/100 g

Degree for Women Sexy Intrigue Antiperspirant and Deodorant PDP and drug facts

Active ingredient Purpose

Aluminum Zirconium Tetrachlorohydrex GLY(17.8%)............anti-perspirant

Warning
For external use only

Do not use on broken skin

Ask a doctor before use if you have kidney disease

Stop use if rash or irritation occurs

Keep out of reach of children. If swallowed, get medical help or contact a Poison Control Center right away.

Inactive ingredients

Cyclopentasiloxane, Stearyl Alcohol, C12-15 Alkyl Benzoate, PPG-14 Butyl Ether, Hydrogenated Castor Oil, Fragrance (Parfum), Dimethicone, Polyethylene, Steareth-100, Helianthus Annuus (Sunflower) Seed Oil, BHT, Zea Mays (Corn) Starch.

Questions?

Call toll-free 1-866-DEGREE1

PACKAGE LABEL

PDP 2.6 oz

PACKAGE LABEL

PDP 1.6 oz

PACKAGE LABEL

PDP 0.5 oz